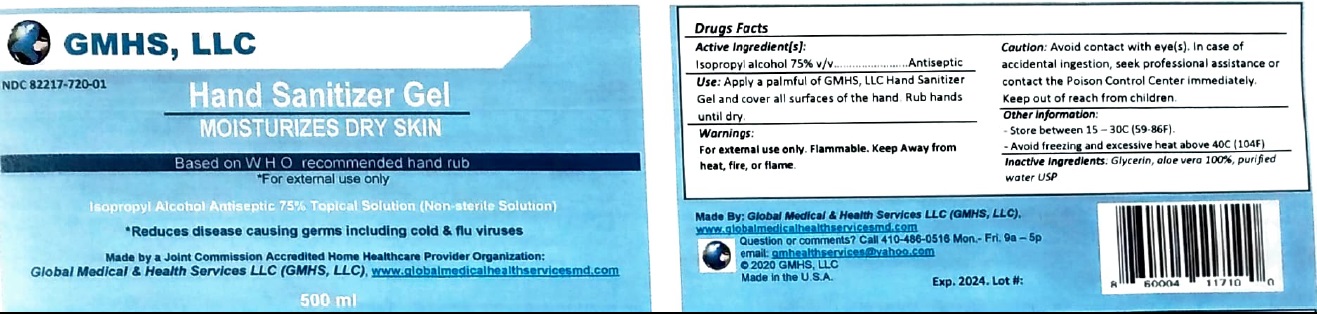 DRUG LABEL: GMHS, LLC Hand Sanitizer
NDC: 82217-720 | Form: GEL
Manufacturer: Global Medical and Health Services, LLC
Category: otc | Type: HUMAN OTC DRUG LABEL
Date: 20230302

ACTIVE INGREDIENTS: ISOPROPYL ALCOHOL 75 mL/100 mL
INACTIVE INGREDIENTS: GLYCERIN; ALOE VERA LEAF; WATER

GMHS, LLC Hand Sanitizer Gel

Active Ingredient[s]:

Isopropyl alcohol 75% v/v

Purpose:

Antiseptic

Use:

Hand sanitizer to reduce disease causing germs including cold & flu viruses

Warnings:

For external use only. Flammable. Keep away from heat, fire, or flame.

Caution: Avoid contact with eye(s). In case of accidental ingestion, seek professional assistance or contact the Poison Control Center immediately.

Keep out of reach from children.

Directions:

Apply a palmful of GMHS, LLC Hand Sanitizer Gel and cover all surfaces of the hand. Rub hands until dry.

Other information:

- Store between 15° - 30°C (59°-86°F).

- Avoid freezing and excessive heat above 40°C (104°F)

Inactive Ingredients:

Glycerin, aloe vera 100%, purified water USP

MOISTURIZES DRY SKIN

Based on WHO recommended hand rub

Isopropyl Alcohol Antiseptic 75% Topical Solution (Non-sterile Solution)

Made by a joint Commission Accredited Home Healthcare Provider Organization:
Global Medical & Health Services LLC (GMHS, LLC), www.globalmedicalhealthservicesmd.com

Question or comments? Call 410-486-0516 Mon. - Fri. 9a - 5p
email: gmhealthservices@yahoo.com
© 2020 GMHS, LLC
Made in the U.S.A.